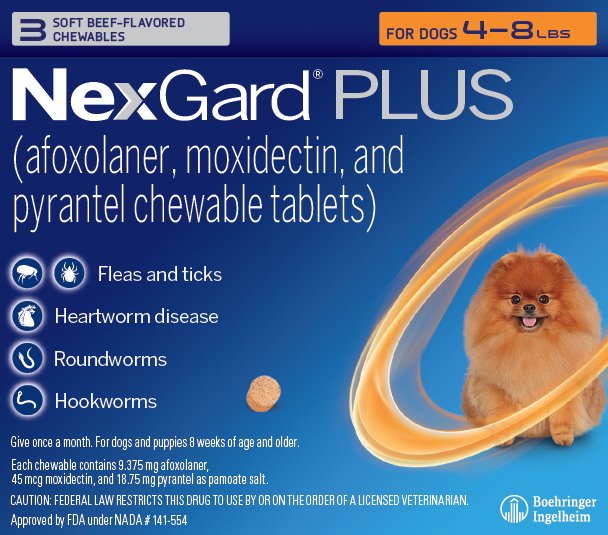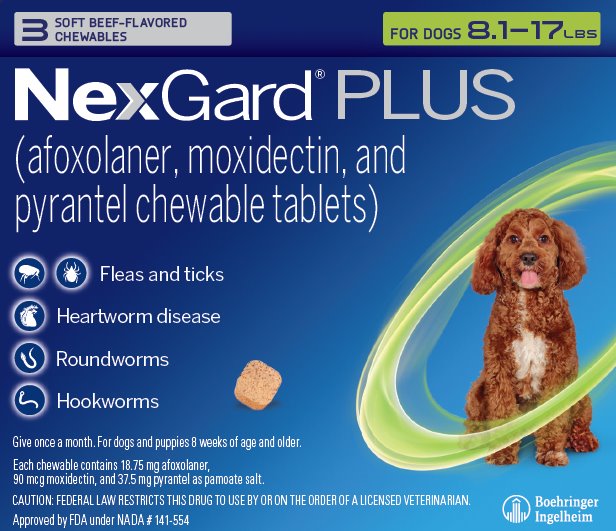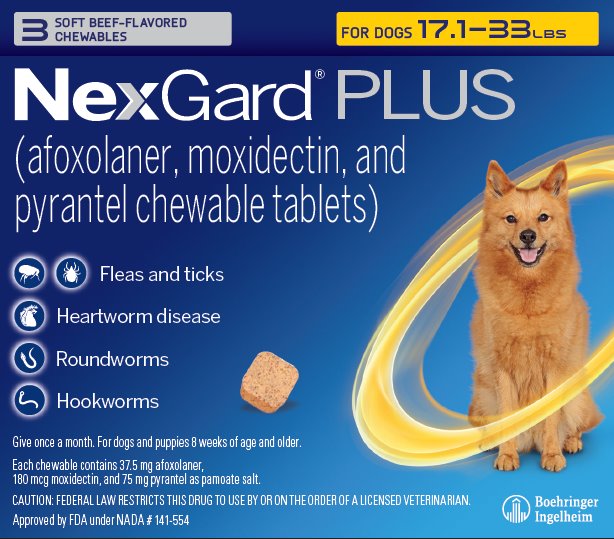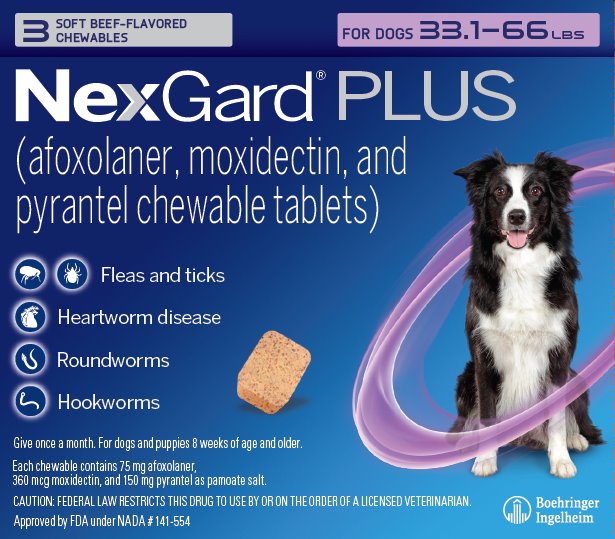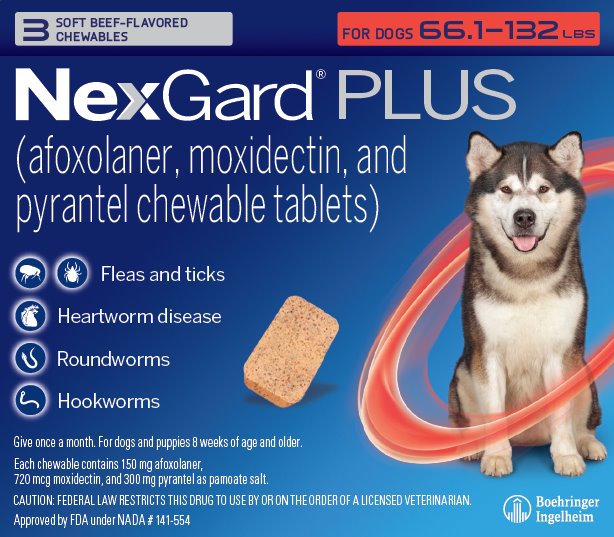 DRUG LABEL: NexGard PLUS
NDC: 0010-4260 | Form: TABLET, CHEWABLE
Manufacturer: Boehringer Ingelheim Animal Health USA Inc.
Category: animal | Type: PRESCRIPTION ANIMAL DRUG LABEL
Date: 20250603

ACTIVE INGREDIENTS: AFOXOLANER 9.375 mg/1 1; MOXIDECTIN 0.045 mg/1 1; PYRANTEL PAMOATE 18.75 mg/1 1

NexGard® PLUS
(afoxolaner, moxidectin, and pyrantel chewable tablets)

For oral use in dogs only

Caution:

Federal law restricts this drug to use by or on the order of a licensed veterinarian.

Description:

NexGard® PLUS (afoxolaner, moxidectin, and pyrantel chewable tablets) is available in five sizes of beef-flavored, soft chewables for oral administration to dogs and puppies according to their weight. Each chewable is formulated to provide minimum doses of 1.14 mg/lb (2.5 mg/kg) afoxolaner, 5.45 mcg/lb (12 mcg/kg) moxidectin, and 2.27 mg/lb (5.0 mg/kg) pyrantel (as pamoate salt).

Afoxolaner is a member of the isoxazoline family of compounds. Its chemical name is 1-Naphthalenecarboxamide,4-[5-[3-chloro-5-(trifluoromethyl)-phenyl]-4,5-dihydro-5-(trifluoromethyl)-3-isoxazolyl]-N-[2-oxo-2-[(2,2,2-trifluoroethyl)amino]ethyl.

Moxidectin is a semisynthetic macrocyclic lactone derived from the actinomycete Streptomycetes cyaneogriseus noncyanogenus. The chemical name for moxidectin is [6R,23E,25S(E)]-5-O-Demethyl-28-deoxy-25-(1,3-dimethyl-1-butenyl)-6,28-epoxy-23-(methoxyimino) milbemycin B.

Pyrantel is a member of the tetrahydropyrimidine family of compounds. Its chemical name is (E)-1,4,5,6-Tetrahydro-1-methyl-2-[2-(2-thienyl) vinyl] pyrimidine 4,4’methylenebis [3-hydroxy-2-naphthoate](1:1).

Indications:

NexGard® PLUS is indicated for the prevention of heartworm disease caused by Dirofilaria immitis and for the treatment and control of adult hookworm (Ancylostoma caninum, Ancylostoma braziliense, and Uncinaria stenocephala) and roundworm (Toxocara canis and Toxascarisleonina) infections. NexGard® PLUS kills adult fleas and is indicated for the treatment and prevention of flea infestations (Ctenocephalides felis) and the treatment and control of Ixodesscapularis (black-legged tick), Rhipicephalus sanguineus (brown dog tick), Dermacentor variabilis (American dog tick), Amblyomma americanum (lone star tick), and Haemaphysalis longicornis (longhorned tick) infestations for one month in dogs and puppies eight weeks of age and older, weighing four pounds of body weight or greater. NexGard® PLUS is indicated for the prevention of Borrelia burgdorferi infections as a direct result of killing Ixodes scapularis vector ticks.

Dosage and Administration:

NexGard® PLUS is given orally once a month at the minimum dosage of 1.14 mg/lb (2.5 mg/kg) afoxolaner, 5.45 mcg/lb (12 mcg/kg) moxidectin, and 2.27 mg/lb (5.0 mg/kg) pyrantel (as pamoate salt).

For heartworm disease prevention, give once monthly for at least six months after last exposure to mosquitoes (see Effectiveness).

Dosing Schedule:

Body; Weight; (lbs.) | Afoxolaner; Per; Chewable; (mg) | Moxidectin; Per; Chewable; (mcg) | Pyrantel*; Per; Chewable; (mg) | Chewables; Administered
4 - 8 | 9.375 | 45 | 18.75 | One
8.1 - 17 | 18.75 | 90 | 37.5 | One
17.1 - 33 | 37.5 | 180 | 75 | One
33.1 - 66 | 75 | 360 | 150 | One
66.1 - 132 | 150 | 720 | 300 | One
Over 132 | Administer the appropriate combination of chewables

*As pamoate salt.

NexGard® PLUS can be administered with or without food. Care should be taken to ensure that the dog consumes the complete dose and that part of the dose is not lost or refused. If a dose is missed, administer NexGard® PLUS and resume a monthly dosing schedule.

Heartworm Prevention:

NexGard® PLUS should be administered at monthly intervals year-round or, at a minimum, administration should start within one month of the dog’s first seasonal exposure to mosquitoes and should continue at monthly intervals until at least six months after the dog’s last exposure (see Effectiveness). When replacing another monthly heartworm preventive product, the first dose of NexGard® PLUS should be given within a month of the last dose of the former medication.

Flea Treatment and Prevention:

NexGard® PLUS should be administered year-round at monthly intervals or started at least one month before fleas become active. To minimize the likelihood of flea reinfestation, it is important to treat all animals within a household with an approved flea control product.

Tick Treatment and Control:

NexGard® PLUS should be administered year-round at monthly intervals or started at least one month before ticks become active.

Intestinal Nematode Treatment and Control:

NexGard® PLUS treats and controls adult hookworms (Ancylostoma caninum, Ancylostoma braziliense, and Uncinaria stenocephala) and roundworms (Toxocara canis and Toxascaris leonina). For the treatment of adult hookworm and roundworm infections, NexGard® PLUS should be administered as a single dose. Monthly use of NexGard® PLUS will control any subsequent infections. Dogs may be exposed to and can become infected with hookworms and roundworms throughout the year, regardless of season or climate.

Contraindications:

There are no known contraindications for the use of NexGard® PLUS.

Warnings:

Not for use in humans. Keep this and all drugs out of the reach of children. In case of accidental ingestion, contact a physician for treatment advice.

Keep NexGard® PLUS in a secure location out of the reach of dogs, cats, and other animals to prevent accidental ingestion or overdose.

Precautions:

Afoxolaner, one of the ingredients in NexGard® PLUS, is a member of the isoxazoline class. This class has been associated with neurologic adverse reactions including tremors, ataxia, and seizures. Seizures have been reported in dogs receiving isoxazoline class drugs, even in dogs without a history of seizures. Use with caution in dogs with a history of seizures or neurologic disorders.

Treatment with fewer than six monthly doses after the last exposure to mosquitoes has not been evaluated and may not provide complete heartworm prevention.

Prior to administration of NexGard® PLUS, dogs should be tested for existing heartworm infection. At the discretion of the veterinarian, infected dogs should be treated with an adulticide to remove adult heartworms. NexGard® PLUS is not effective against adult D. immitis.

The safe use of NexGard® PLUS in breeding, pregnant, or lactating dogs has not been evaluated.

Adverse Reactions:

In a field safety and effectiveness study, NexGard® PLUS was administered to dogs for the prevention of heartworm disease. The study included a total of 272 dogs (134 administered NexGard® PLUS and 138 administered active control) treated once monthly for 11 treatments. Over the 330-day study period, all observations of potential adverse reactions were recorded. The most frequent reactions reported in the NexGard® PLUS group are presented in the following table.

Table 1. Dogs With Adverse Reactions

Clinical Sign | NexGard® PLUS; n = 134; Number (Percentage) | Active Control; n = 138; Number (Percentage)
Diarrhea | 9 (6.7%) | 7 (5.1%)
Vomiting | 6 (4.5%) | 7 (5.1%)
Lethargy | 3 (2.2%) | 5 (3.6%)
Itching | 3 (2.2%) | 3 (2.2%)
Dermatitis | 2 (1.5%) | 1 (0.7%)
Anorexia | 1 (0.7%) | 4 (2.9%)
Muscle tremor | 1 (0.7%) | 1 (0.7%)

One dog in the NexGard® PLUS group was reported to exhibit muscle tremors along with nausea and depression for one day after the Day 0 treatment. The dog remained in the study and muscle tremors were not reported after any subsequent treatments.

Contact Information:

For a copy of the Safety Data Sheet (SDS) or to report suspected adverse drug events, contact Boehringer Ingelheim Animal Health USA Inc. at 1-888-637-4251 or www.nexgardforpets.com.

For additional information about adverse drug experience reporting for animal drugs, contact FDA at 1-888-FDA-VETS or www.fda.gov/reportanimalae.

Clinical Pharmacology:

Mode of Action:

NexGard® PLUS (afoxolaner, moxidectin, and pyrantel chewable tablets) contains the three active pharmaceutical ingredients afoxolaner, moxidectin, and pyrantel (as pamoate salt).

Afoxolaner is a member of the isoxazoline family, shown to bind at a binding site to inhibit insect and acarine ligand-gated chloride channels, in particular those gated by the neurotransmitter gamma-aminobutyric acid (GABA), thereby blocking pre- and postsynaptic transfer of chloride ions across cell membranes. Prolonged afoxolaner-induced hyperexcitation results in uncontrolled activity of the central nervous system and death of insects and acarines. The selective toxicity of afoxolaner between insects and acarines and mammals may be inferred by the differential sensitivity of the insects and acarines’ GABA receptors versus mammalian GABA receptors.

Moxidectin is an endectocide in the macrocyclic lactone class. Moxidectin acts by interfering with chloride channel-mediated neurotransmission in susceptible parasites, which results in paralysis and death of the parasite.

Pyrantel is a nematocide belonging to the tetrahydropyrimidine class. Pyrantel acts as a depolarizing, neuromuscular-blocking agent in susceptible parasites, causing paralysis and death or expulsion of the parasite.

Pharmacokinetics:

Following a single oral administration of a near-final formulation of NexGard® PLUS (at mean doses of 3.9 mg/kg afoxolaner, 18.8 mcg/kg moxidectin, and 7.8 mg/kg pyrantel pamoate) in fed and fasted Beagle dogs (10 to 21 months of age), afoxolaner and moxidectin were more rapidly absorbed in the fasted state with a time to maximum concentration (Tmax) of 2 to 3 hours. The afoxolaner mean maximum plasma concentrations (Cmax) in the fed and fasted states were 1610 and 2200 ng/mL (CV=33 and 16%) and the moxidectin mean Cmax values were 11.1 and 15.5 ng/mL (CV=39 and 24%), respectively. The area under the curve (AUC) for afoxolaner and moxidectin were similar between fed and fasted states. Post-dose pyrantel plasma concentrations were quantifiable out to 24 hours.

Following six oral administrations of NexGard® PLUS at 1, 3, and 5X the maximum exposure dose of 5 mg/kg, 24 mcg/kg, and 10 mg/kg afoxolaner, moxidectin, and pyrantel pamoate, respectively, every 28 days in 8-week-old Beagle dogs, afoxolaner and moxidectin Tmax ranged from 2 to 6 hours. The observed mean Cmax and AUC at steady state in the 1X dose group were 2230 ng/mL and 19000 days*ng/mL for afoxolaner and 14.8 ng/mL and 55.2 days*ng/mL for moxidectin, respectively. Based on mean Cmin, afoxolaner and moxidectin accumulated by less than 4-fold at steady state. Afoxolaner and moxidectin exposure increased in a dose proportional manner between the 1X and 3X dose groups but was less than dose proportional in the 5X dose group.

Pyrantel pamoate is poorly absorbed into systemic circulation. Pyrantel pamoate is intended to remain in the gastrointestinal tract to allow effective concentrations to be delivered to gastrointestinal nematodes.

Effectiveness:

Heartworm Prevention:

In two well-controlled laboratory studies, NexGard® PLUS was 100% effective against induced D. immitis infections when administered for six consecutive months.

In a well-controlled US field study consisting of 120 dogs administered NexGard® PLUS and 124 administered an active control, no dogs treated with NexGard® PLUS tested positive for heartworm disease. All dogs treated with NexGard® PLUS were negative for D. immitis antigen and blood microfilariae at study completion on Day 330.

Flea Treatment and Prevention:

In a well-controlled laboratory study, NexGard® PLUS demonstrated ≥99.8% effectiveness against adult fleas 24 hours after weekly infestations for one month.

In a separate well-controlled laboratory study, afoxolaner alone began to kill fleas four hours after initial administration and demonstrated >99% effectiveness at eight hours.

In an additional well-controlled laboratory study, afoxolaner alone demonstrated 100% effectiveness against adult fleas 24 hours post-infestation for 35 days and was ≥93% effective at 12 hours post-infestation through Day 21 and on Day 35. On Day 28, afoxolaner alone was 81.1% effective 12 hours post-infestation. Dogs in both the afoxolaner-treated and control groups that were infested with fleas on Day -1 generated flea eggs at 12 and 24 hours post-treatment (0-11 eggs and 1-17 eggs in the afoxolaner-treated dogs, and 4-90 eggs and 0-118 eggs in the control dogs, at 12 and 24 hours, respectively). At subsequent evaluations post-infestation, fleas from dogs in the afoxolaner-treated group were essentially unable to produce any eggs (0-1 eggs), while fleas from dogs in the control group continued to produce eggs (1-141 eggs).

In a 90-day US field study conducted in households with existing flea infestations of varying severity, the effectiveness of afoxolaner alone against fleas on the Day 30, 60, and 90 visits compared with baseline was 98.0%, 99.7%, and 99.9%, respectively. In a second 90-day US field study, the effectiveness of afoxolaner alone against fleas on the Day 30, 60, and 90 visits compared with baseline was 97.5%, 99.7%, and 99.9%, respectively. Dogs in the second study with signs of Flea Allergy Dermatitis (FAD) showed improvement in erythema, alopecia, papules, scales, crusts, and excoriation following treatment, as a direct result of eliminating fleas.

Collectively, the data from the five studies (three laboratory and two field) demonstrate that NexGard® PLUS kills fleas before they can lay eggs, thus preventing subsequent flea infestations after the start of treatment of existing flea infestations.

Tick Treatment and Control:

In well-controlled laboratory studies, NexGard® PLUS demonstrated ≥97% effectiveness against Amblyomma americanum 72 hours post-infestation, for one month.

In well-controlled laboratory studies, a chewable containing afoxolaner alone, one of the active ingredients in NexGard® PLUS, demonstrated effectiveness against Ixodes scapularis, Rhipicephalus sanguineus, and Dermacentor variabilis at 48 hours post-infestation, and against Haemaphysalis longicornis at 72 hours post-infestation, for one month.

In two additional well-controlled laboratory studies, NexGard® PLUS was effective at preventing Borrelia burgdorferi infections after dogs were infested with Ixodes scapularis vector ticks 28 days post-treatment.

Intestinal Nematode Treatment and Control:

Elimination of adult roundworms (Toxocara canis and Toxascaris leonina) and hookworms (Ancylostoma caninum, Ancylostoma braziliense, and Uncinaria stenocephala) was demonstrated in well-controlled laboratory studies.

Target Animal Safety:

Margin of Safety:

NexGard® PLUS was administered orally at 1, 3, and 5X the maximum exposure doses at approximately 28-day intervals for six treatments to 8-week-old Beagle puppies. Dogs in the control group were sham-dosed. There were no clinically relevant, treatment-related effects on body weights, food consumption, clinical pathology (hematology, coagulation, serum chemistry, and urinalysis), gross pathology, histopathology, organ weights, or ophthalmic examinations. Mild, self-limiting diarrhea (with and without blood) was possibly related to treatment, as there were more incidences in the NexGard® PLUS groups than the control group throughout the study, including within 48 hours after treatment.

Avermectin-Sensitive Collie Safety:

NexGard® PLUS was administered orally at 1, 3, and 5X the maximum label dose to MDR1-deficient Collies once on Day 0, with a second administration to the 1X group on Day 28. Dogs in the control group were sham-dosed on Days 0 and 28. No clinical signs of avermectin toxicity were noted in any dog at any time during the study. Vomiting was observed in some dogs in the 3X and 5X groups and resolved without treatment. Diarrhea, with or without blood, was observed in some dogs in all of the NexGard® PLUS groups and resolved without treatment.

Heartworm-Positive Safety:

NexGard® PLUS was administered orally at 1X and 3X the maximum exposure doses at approximately 28-day intervals for three treatments to Beagle dogs with adult heartworm infections and circulating microfilariae. Dogs in the control group were sham-dosed. Diarrhea was observed in one dog in the 1X group and in three dogs in the 3X group, and vomiting was observed in two dogs in the 3X group. No signs of avermectin toxicity were observed at any time during the study. There were no clinical signs associated with death of the microfilariae observed in any of the dogs.

Field Safety:

In a well-controlled field study, NexGard® PLUS was used concurrently with other medications such as vaccines, antibiotics, non-steroidal anti-inflammatory drugs (NSAIDs), anesthetics, sedatives, analgesics, steroids, anthelmintics, antiemetics, and antipruritics. No adverse reactions were associated with the concurrent use of NexGard® PLUS and other medications.

How Supplied:

NexGard® PLUS is available in five strengths of beef-flavored soft chewables formulated according to the weight of the dog (see Dosage and Administration). Each chewable size is available in color-coded packages of 1, 3, or 6 chewables.

Storage Information:

Store in original package at or below 25°C (77°F) with excursions permitted up to 40°C (104°F).

Approved by FDA under NADA # 141-554

Marketed by: Boehringer Ingelheim Animal Health USA Inc., Duluth, GA 30096

NEXGARD® is a registered trademark of Boehringer Ingelheim Animal Health France, used under license.

©2024 Boehringer Ingelheim Animal Health USA Inc. All rights reserved.

181531-005

Rev. 10/2024